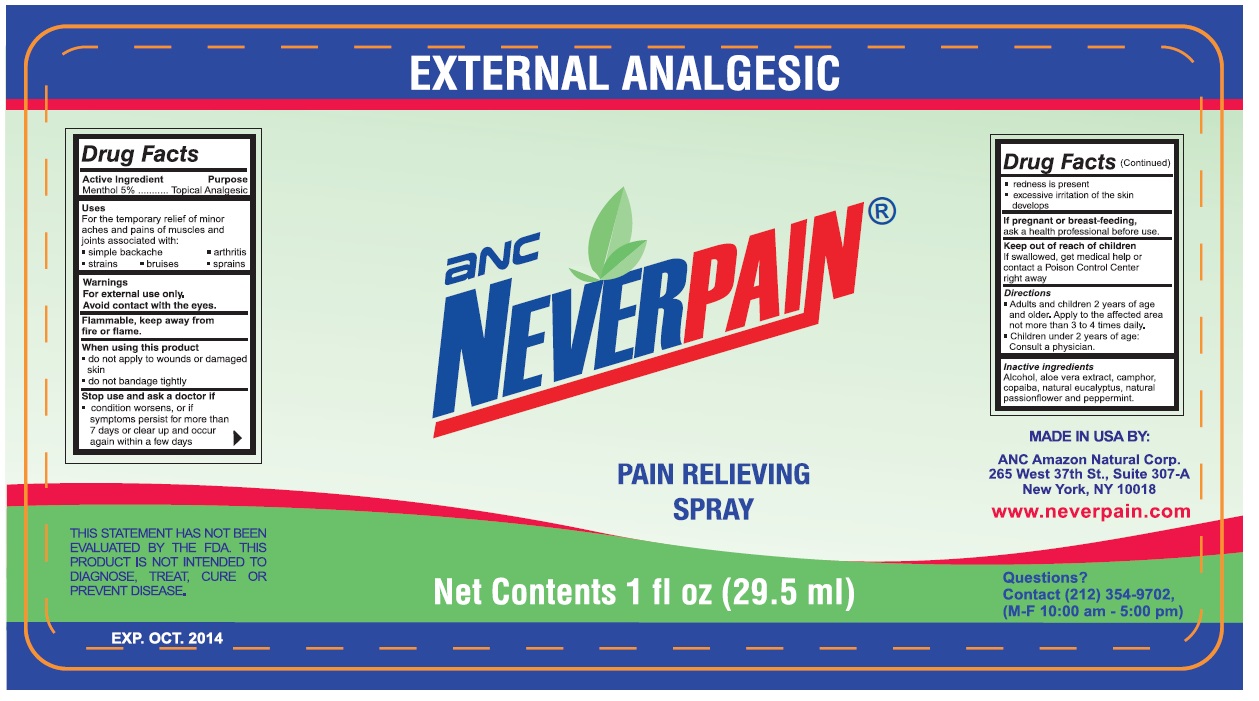 DRUG LABEL: Neverpain
NDC: 75974-200 | Form: SPRAY
Manufacturer: ANC Amazon Natural Corp.
Category: otc | Type: HUMAN OTC DRUG LABEL
Date: 20170202

ACTIVE INGREDIENTS: MENTHOL, UNSPECIFIED FORM 5 g/100 mL
INACTIVE INGREDIENTS: ALCOHOL; ALOE VERA LEAF; CAMPHOR (SYNTHETIC); COPAIFERA OFFICINALIS RESIN; EUCALYPTUS GUM; PASSIFLORA INCARNATA FLOWER; PEPPERMINT

Neverpain

ANC NEVERPAIN

FOR EXTERNAL USE ONLY

Neverpain is a natural, deep penetrating, fast acting pain reliever free of suspected carcinogens and coloring agents. It is a nutrient in bone and muscle tissue.

Neverpain is for the temporary relief of minor aches and pains of muscles and joints associated with: simple backache, arthritis, strains, bruises and sprains.

Drug Facts

Active Ingredient

Menthol 5%

Purpose

Topical Analgesic

Uses

For the temporary relief of minor aches and pains of muscles and joints associated with:

▪ simple backache

▪ arthritis

▪ strains

▪ bruises

▪ sprains

Warnings
For external use only.

Avoid contact with the eyes.

STORAGE AND HANDLING

Flammable, keep away from fire or flame.

When using this product
▪ do not apply to wounds or damaged skin
▪ do not bandage tightly

Stop use and ask a doctor if

- condition worsens, or if symptoms persist for more than 7 days or clear up and occur again within a few days.
- redness is present.
- excessive irritation of the skin develops.

PREGNANCY OR BREAST FEEDING

If pregnant or breast-feeding, ask a health professional before use.

Keep out of reach of children
If swallowed, get medical help or contact a Poison Control Center right away

Directions

- Adults and children 2 years of age and older. Apply to the affected area not more than 3 to 4 times daily.
- Children under 2 years of age: Consult a physician.

Inactive ingredients
Alcohol, aloe vera extract, camphor, copaiba, natural eucalyptus, natural passionflower and peppermint,

Do not contain steroids

Questions?
Contact (212) 354-9702,
(M-F 10:00 am - 5:00 pm)

NDC: 75974-200-01 & 75974-200-03

MADE IN USA BY

ANC Amazon Natural Corp.
265 W. 37th St., Suite 307-A
New York, NY 10018

www.neverpain.com

PACKAGE LABEL

EXTRA STRENGTH

EXTERNAL ANALGESIC

NEVERPAIN

SPRAY